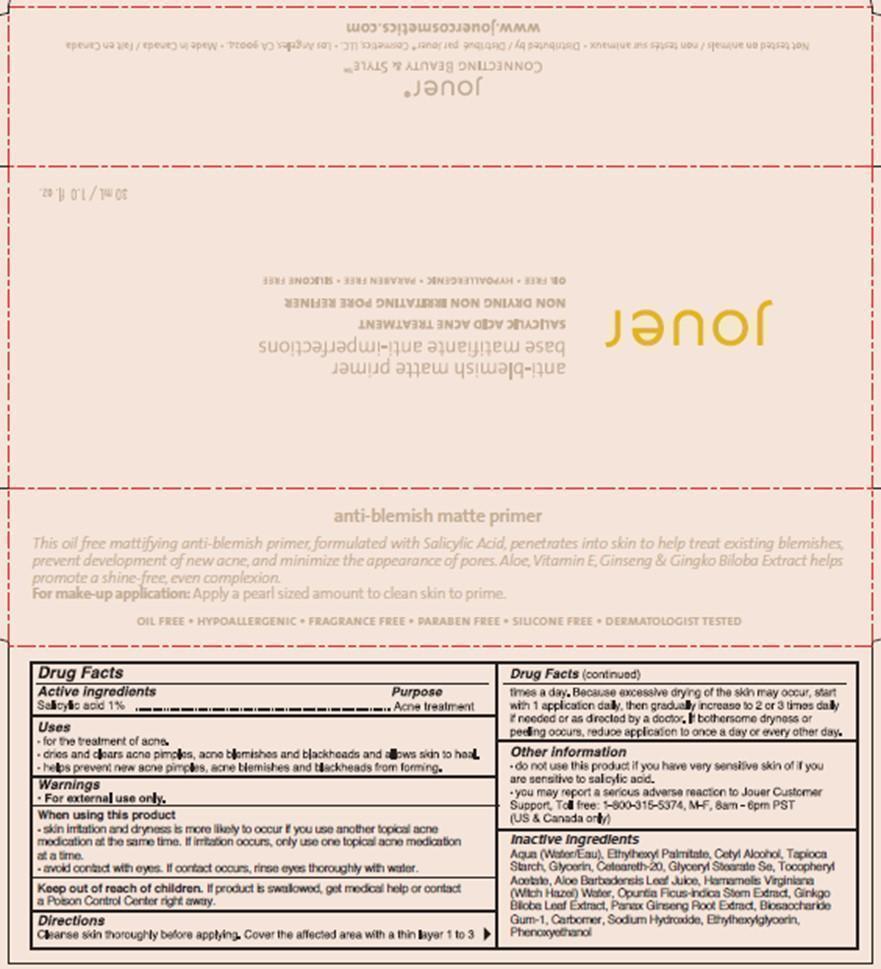 DRUG LABEL: ANTI-BLEMISH MATTE PRIMER
NDC: 69017-101 | Form: LOTION
Manufacturer: Jouer Cosmetics LLC
Category: otc | Type: HUMAN OTC DRUG LABEL
Date: 20140621

ACTIVE INGREDIENTS: SALICYLIC ACID 1 mg/100 mL
INACTIVE INGREDIENTS: WATER; ETHYLHEXYL PALMITATE; CETYL ALCOHOL; STARCH, TAPIOCA; GLYCERIN; POLYOXYL 20 CETOSTEARYL ETHER; GLYCERYL STEARATE SE; .ALPHA.-TOCOPHEROL ACETATE, DL-; ALOE VERA LEAF; HAMAMELIS VIRGINIANA LEAF WATER; OPUNTIA FICUS-INDICA STEM; GINKGO; ASIAN GINSENG; BIOSACCHARIDE GUM-1; CARBOMER HOMOPOLYMER TYPE A (ALLYL PENTAERYTHRITOL CROSSLINKED); SODIUM HYDROXIDE; ETHYLHEXYLGLYCERIN; PHENOXYETHANOL

PACKAGE LABEL

Jouer

Anti-blemish matte primer

Base matifiante anti-imperfections

SALICYLIC ACID ACNE TREATMENT

NON DRYING NO IRRITATING PORE REFINER

OIL FREE – HYPOALLERGENE-PARABEN FREE-SILICONE FREE

30 mL / 1.0 fl. oz.

PACKAGE LABEL

Jouer

CONNECTIONG BEAUTY & STYLE

Not tested on animals / non testes animaux- Distributed by / distribue par Jouer Cosmetics LLC- Los Angeles Ca 90024- Made in Canada / Fait en Canada

WWW.JOUERCOSMETICS.COM

PACKAGE LABEL

Anti-blemish matte primer

This oil free mattifying anti-blemish primer, formulated with Salicylic Acid, penetrates into skin to help treat existing blemishes. Prevent development of new acne, and minimize the appearance of pores. Aloe, Vitamin E, Ginseng & Gingko Biloba Extract helps promote a shine-free, even complexion.

For make-up application: Apply a pearl sized amount to clean skin to prime.

OIL FREE-HYPOALLERGENIC-FRAGRANCE FREE-PARABEN FREE-SILICONE FREE-DERMATOLOGIST TESTED

Drug Facts

Active ingredients

Salicylic acid 1%

Purpose

Acne treatment

Uses

- for the treatment of acne.

- dries and clears acne pimples, acne blemishes and blackheads and allows skin to heal.

-helps prevent new acne pimples, acne blemishes and blackheads from forming.

Warnings

WARNINGS

For external use only.

When using this product

-skin irritation and dryness is more likely to occur if you use another topical acne medication at the same time. If irritation occurs, only use one topical acne medication at all a time.

-avoid contact with eyes. If contact occurs, rinse eyes thoroughly with water.

Keep out of reach of children. If product is swallowed, get medical help or contact a poison control center right away.

Directions

Cleanse skin thoroughly before applying. Cover the affected area with a thin layer 1 to 3 times a day. Because excessive drying of the skin may occur, start with 1 application daily, then gradually increase to 2 or 3 times daily if needed or as directed by a doctor. If bothersome dryness or peeling occurs, reduce application to once a day or every other day.

Other information

-do not use this product if you have very sensitive skin of if you are sensitive to salicylic acid.

ADVERSE REACTIONS

-you may report a serious adverse reaction to Jouer customer support, toll free: 1-800-315-5374, M-F, 8am-6pm PST (US & Canada only)

Inactive ingredients

Aqua (water / Eau), Ethylhexyl Palmitate, Cetyl Alcohol, Tapioca Starch, Glycerin, Ceteareth-20, Glyceryl Stearate Se, Tocopheryl Acetate, Aloe Barbadensis Leaf Juice, Hamamelis Virginiana (Witch Hazel) Water, Opuntia Ficus-indica Stem Extract, Biosaccharide Gum-1, Carbomer, Sodium Hydroxide, Ethylhexylglycerin, Phenoxyethanol